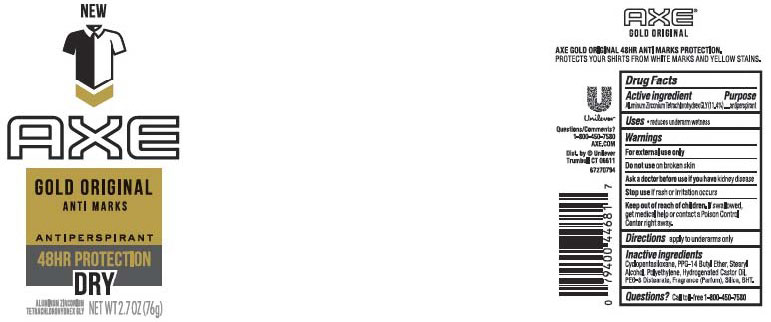 DRUG LABEL: Axe
NDC: 64942-1522 | Form: STICK
Manufacturer: Conopco Inc. d/b/a/ Unilever
Category: otc | Type: HUMAN OTC DRUG LABEL
Date: 20211201

ACTIVE INGREDIENTS: ALUMINUM ZIRCONIUM TETRACHLOROHYDREX GLY 11.4 g/100 g
INACTIVE INGREDIENTS: CYCLOMETHICONE 5; HYDROGENATED CASTOR OIL; BUTYLATED HYDROXYTOLUENE; PPG-14 BUTYL ETHER; STEARYL ALCOHOL; PEG-8 DISTEARATE; SILICON DIOXIDE; HIGH DENSITY POLYETHYLENE

Axe Gold Original Antiperspirant

AXE GOLD ORIGINAL ANTIPERSPIRANT - aluminum zirconium tetrachlorohydrex gly stick

Axe Gold Original Antiperspirant

Drug Facts

Active ingredient

Aluminum Zirconium Tetrachlorohydrex GLY (11.4 %)

Purpose

antiperspirant

Uses

• reduces underarm wetness

Warnings

• For external use only.
• Do not use on broken skin .
• Ask a doctor before use if you have kidney disease.
• Stop use if rash or irritation occurs.

• Keep out of reach of children.

If swallowed, get medical help or contact a Poison Control Center right away.

Directions

apply to underarms only

Inactive ingredients

Cyclopentasiloxane, Stearyl Alcohol, PPG-14 Butyl Ether, Hydrogenated Castor Oil, Talc, PEG-8 Distearate, Fragrance (Parfum), BHT

Questions?

Call toll-free 1-800-450-7580